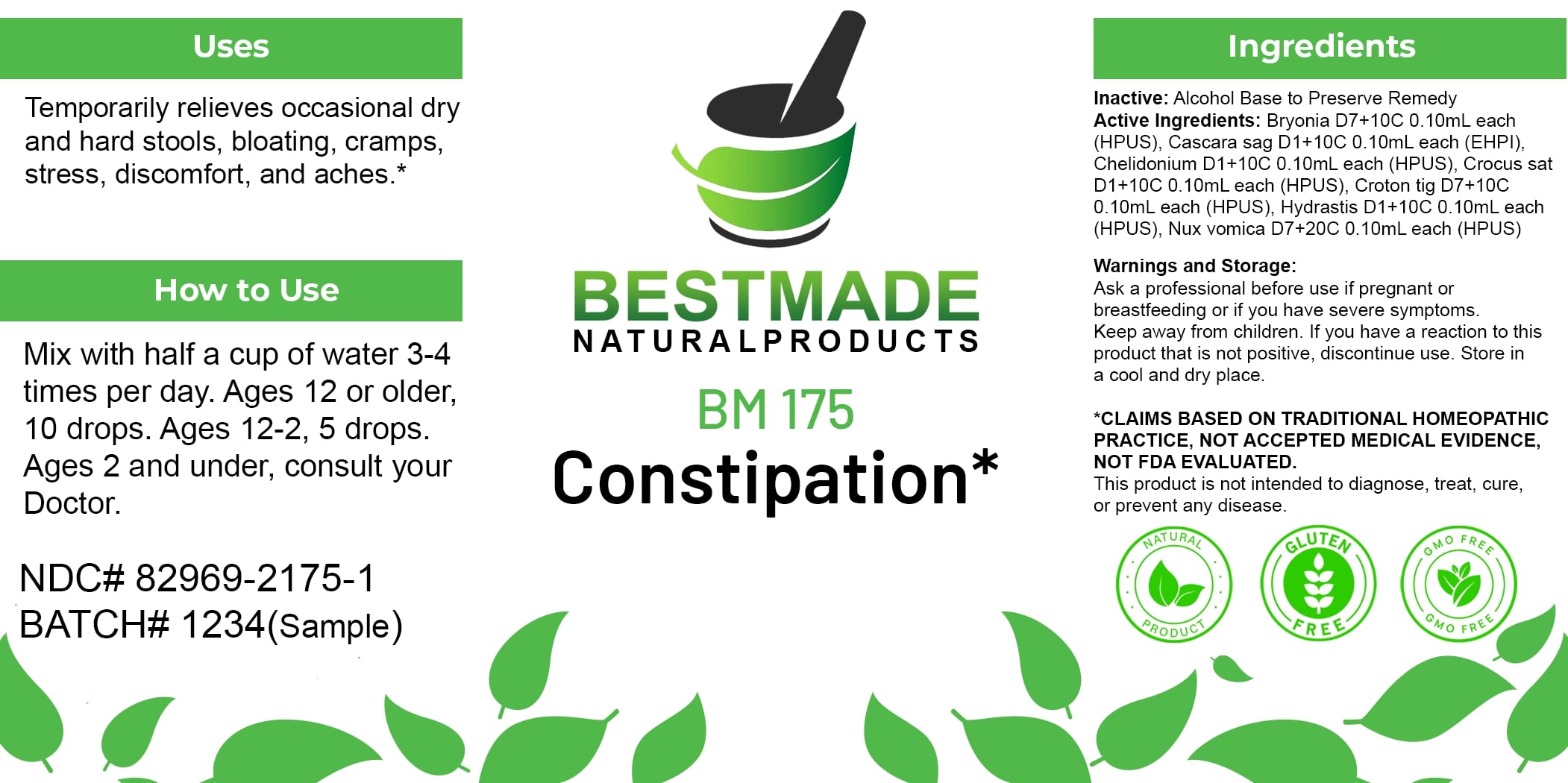 DRUG LABEL: Bestmade Natural Products BM175
NDC: 82969-2175 | Form: LIQUID
Manufacturer: Bestmade Natural Products
Category: homeopathic | Type: HUMAN OTC DRUG LABEL
Date: 20250219

ACTIVE INGREDIENTS: GOLDENSEAL 30 [hp_C]/30 [hp_C]; CHELIDONIUM MAJUS 30 [hp_C]/30 [hp_C]; CROTON TIGLIUM SEED 30 [hp_C]/30 [hp_C]; BRYONIA ALBA ROOT 30 [hp_C]/30 [hp_C]; SAFFRON 30 [hp_C]/30 [hp_C]; STRYCHNOS NUX-VOMICA SEED 30 [hp_C]/30 [hp_C]; FRANGULA PURSHIANA BARK 30 [hp_C]/30 [hp_C]
INACTIVE INGREDIENTS: ALCOHOL 30 [hp_C]/30 [hp_C]

BM175

DOSAGE AND ADMINISTRATION

How to Use

Mix with half a cup of water 3-4 times per day. Ages 12 or older, 10 drops. Ages 12-2, 5 drops. Ages 2 and under, consult your Doctor.

INACTIVE INGREDIENT

Ingredients

Inactive: Alcohol Base to Preserve Remedy

ACTIVE INGREDIENT

Active Ingredients: Bryonia D7+10C 0.10ml each (HPUS), Cascara sag D1+10C 0.10ml each (EHP), Chelidonium D1+10C 0.10ml each (HPUS), Crocus sat D1+10C 0.10ml each (HPUS), Croton tig D7+10C 0.10ml each (HPUS), Hydrastis C1+10C 0.10ml each (HPUS), Nux vomica D7+20C 0.10ml each (HPUS)

Uses

Temporarily relieves occasional dry and hard stools, bloating, cramps, stress, discomfort, and aches.*

*CLAIMS BASED ON TRADITIONAL HOMEOPATHIC PRACTICE. NOT ACCEPTED MEDICAL EVIDENCE. NOT FDA EVALUATED.

This product is not intended to diagnose, treat, cure, or prevent any disease.

Uses

Temporarily relieves occasional dry and hard stools, bloating, cramps, stress, discomfort, and aches.*

*CLAIMS BASED ON TRADITIONAL HOMEOPATHIC PRACTICE. NOT ACCEPTED MEDICAL EVIDENCE. NOT FDA EVALUATED.

This product is not intended to diagnose, treat, cure, or prevent any disease.

KEEP OUT OF REACH OF CHILDREN

Warnings and Storage:

Ask a professional before use if pregnant or breastfeeding or if you have severe symptoms. Keep away from children. If you have a reaction to this product that is not positive, discontinue use. Store in a cool and dry place.

Warnings and Storage:

Ask a professional before use if pregnant or breastfeeding or if you have severe symptoms. Keep away from children. If you have a reaction to this product that is not positive, discontinue use. Store in a cool and dry place.

*CLAIMS BASED ON TRADITIONAL HOMEOPATHIC PRACTICE. NOT ACCEPTED MEDICAL EVIDENCE. NOT FDA EVALUATED.

This product is not intended to diagnose, treat, cure, or prevent any disease.

Entire package label